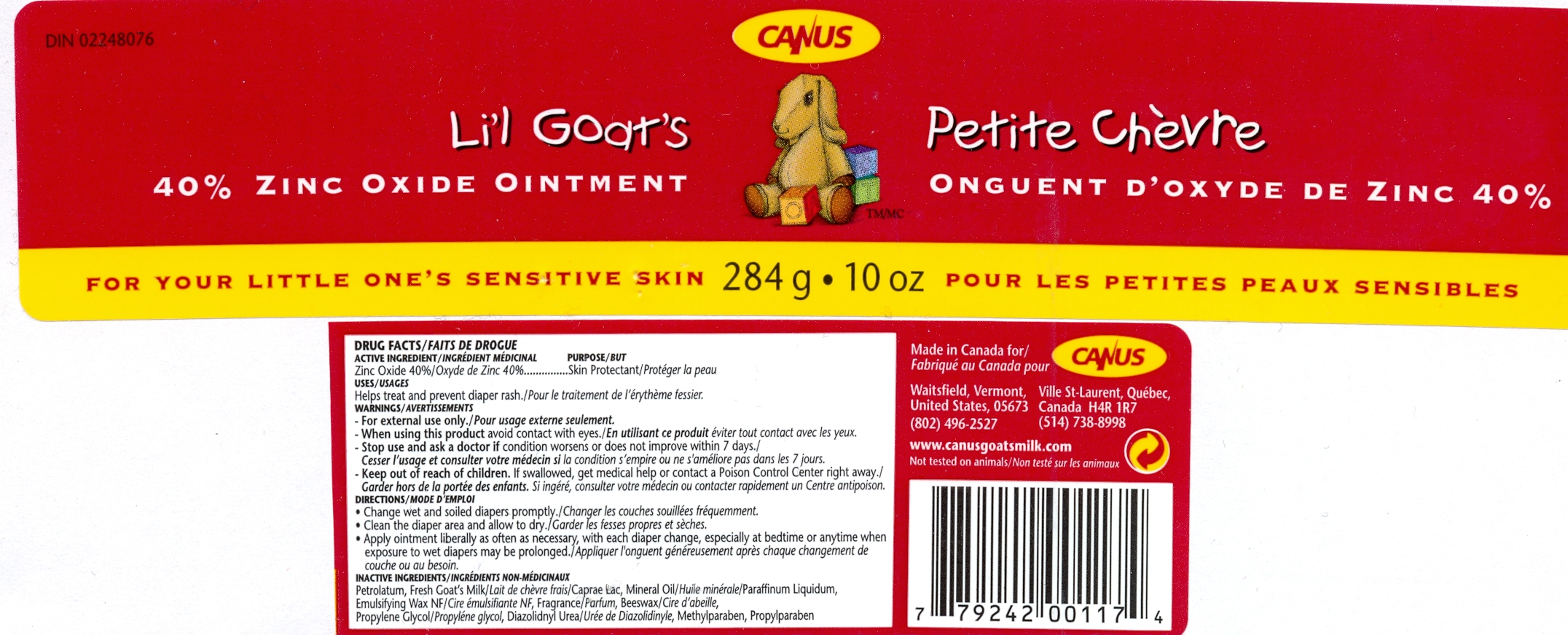 DRUG LABEL: Lil Goats Zinc Oxide
NDC: 10100-117 | Form: OINTMENT
Manufacturer: Canus Vermont LLC
Category: otc | Type: HUMAN OTC DRUG LABEL
Date: 20111216

ACTIVE INGREDIENTS: ZINC OXIDE 113.6 g/284 g
INACTIVE INGREDIENTS: PETROLATUM; MINERAL OIL; APIS MELLIFERA; GOAT MILK

Canus Li'l Goat's 40% Zinc Oxide Ointment

ACTIVE INGREDIENT

Zinc Oxide.......40.0%..........Skin Protectant

PURPOSE

Use: Reduces underarm perspiration - Extra effective

PURPOSE

Helps treat and prevent diaper rash

WARNINGS

For External use only - When using this product avoid contact with eyes

Keep out of reach of children.

GENERAL PRECAUTIONS

If swallowed, get medical help or contact a poison control center right away.

Ask a doctor if condition worsens or does not improve within 7 days.

DOSAGE AND ADMINISTRATION

Directions change wet and soiled diapers promptly. Clean the diaper area and allow to dry. Apply ointment liberally as often as necessary, with each diaper change, especially at bedtime or anytime when exposure to wet diapers may be prolonged..

INACTIVE INGREDIENT

Petrolatum, Fresh goat's milk, mineral oil, emulsifying wax NF, parfum, beeswax, propylene glycol and diazolicinyl urea and methylparaben and propylparaben.

INDICATIONS AND USAGE

Skin Protectant

QUESTIONS

www.canusgoatsmilk.com

HOW SUPPLIED

Made in Canada for: Waitsfield, Vermont, United States, 05673 tel; 802-496-2527 and Ville St-Laurent, Québec, Canada H4R 1R7 tel: 514-738-8998

Not tested on animals.